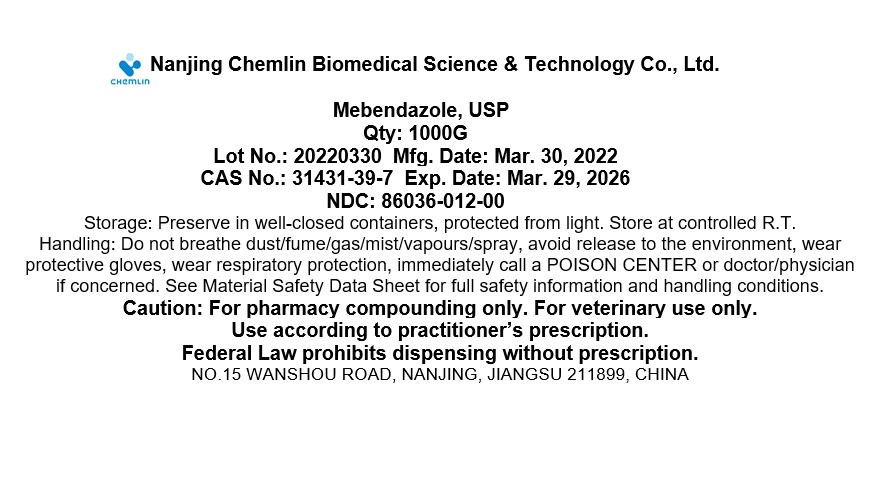 DRUG LABEL: Mebendazole
NDC: 86036-012 | Form: POWDER
Manufacturer: Nanjing Chemlin Biomedical Science & Technology Co, Ltd.
Category: other | Type: BULK INGREDIENT - ANIMAL DRUG
Date: 20240816

ACTIVE INGREDIENTS: MEBENDAZOLE 1 g/1 g

Mebendazole

Mebendazole

<p class="First"><img id="L32d20b12-67f7-4ebe-954f-90605439c599" src="/validator-lite/validator/spl/8fadae45-2c1d-4706-bfc9-a97476376fcb/Label of Mebendazole.jpg?useSession=true" alt="" data-mce-src="../validator/spl/8fadae45-2c1d-4706-bfc9-a97476376fcb/Label of Mebendazole.jpg?useSession=true"></p>